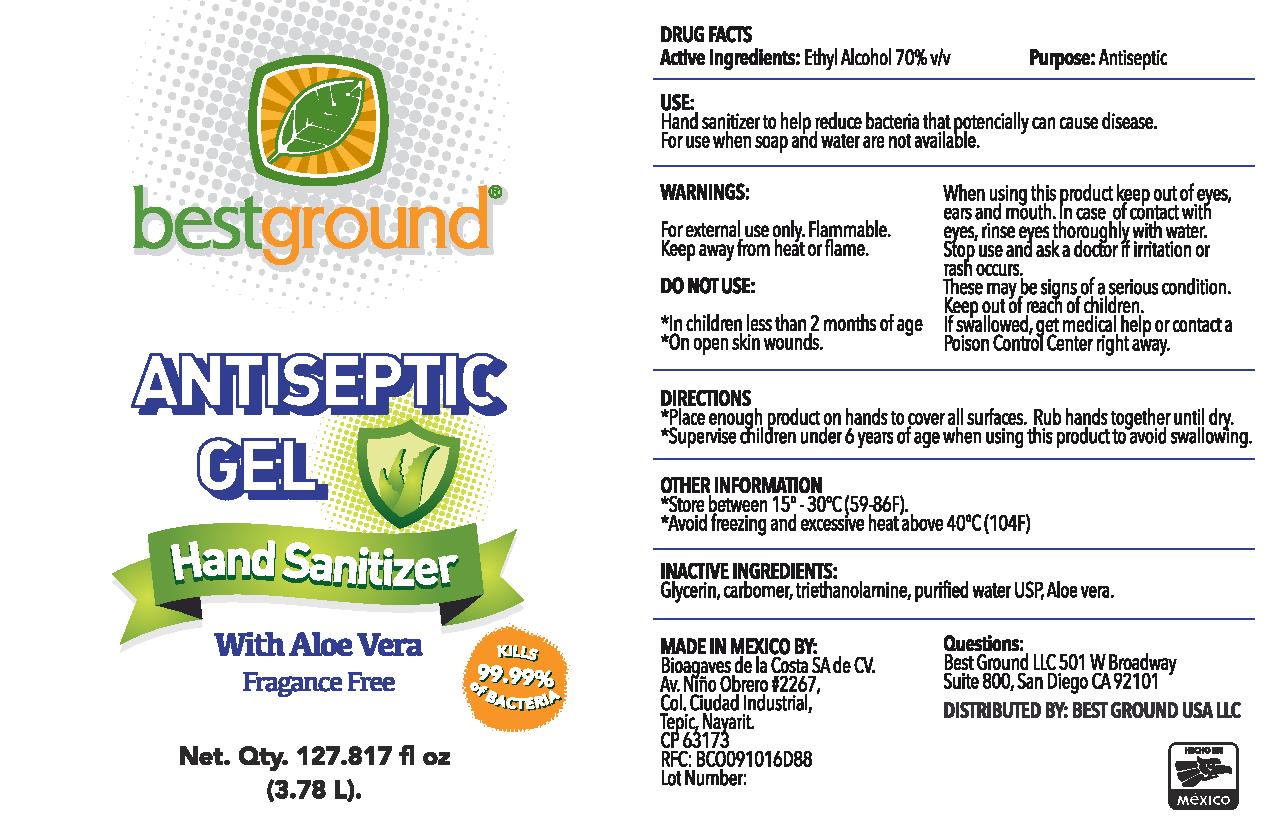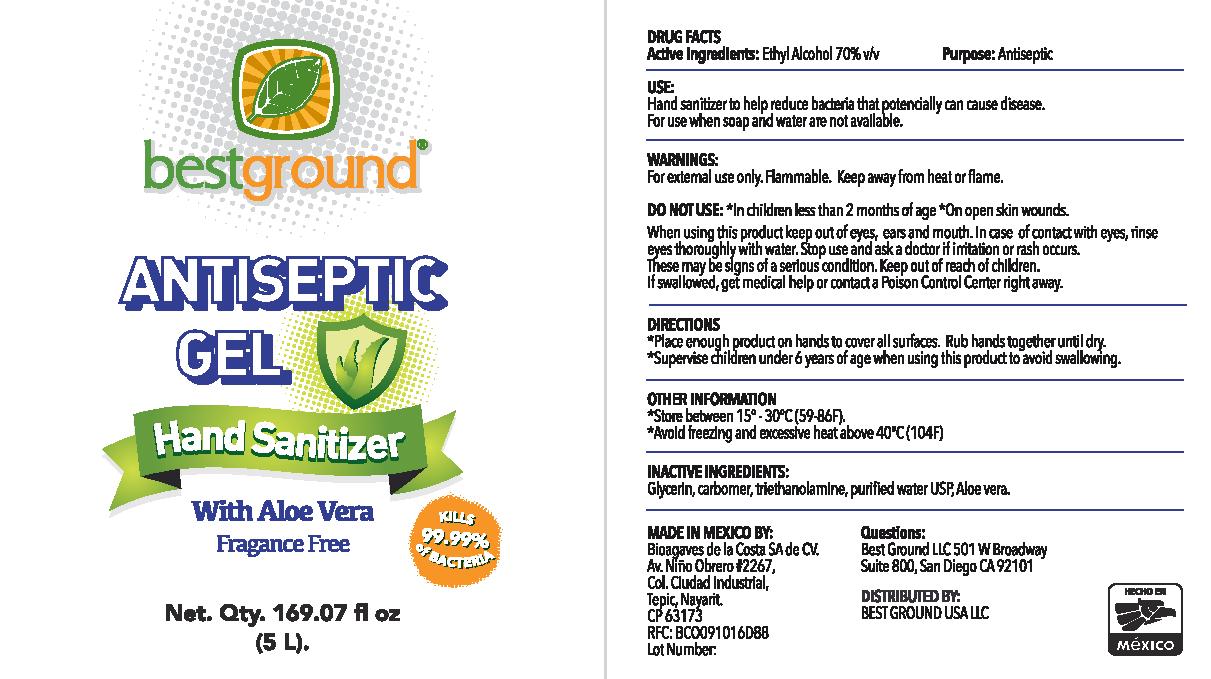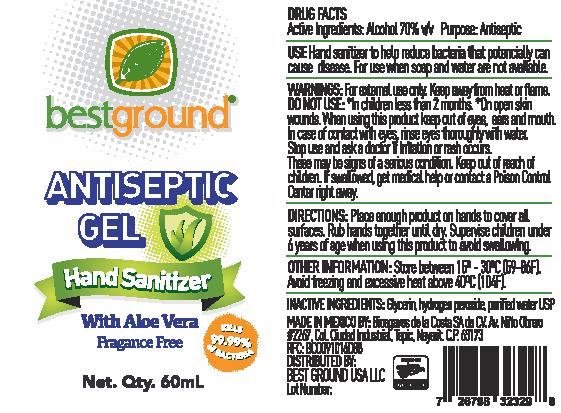 DRUG LABEL: Antiseptic Gel Hand Sanitizer
NDC: 76598-004 | Form: GEL
Manufacturer: Bioagaves de la Costa, S.A. de C.V.
Category: otc | Type: HUMAN OTC DRUG LABEL
Date: 20200903

ACTIVE INGREDIENTS: ALCOHOL 70 mL/100 mL
INACTIVE INGREDIENTS: TROLAMINE; GLYCERIN; CARBOMER 940; ALOE VERA LEAF; WATER

Active Ingredients

Ethyl Alcohol 80% v/v

Purpose

Antiseptic

Use

Hand sanitizer to help reduce bacteria that can potencially cause disease.

For use when soap and water are not available.

WARNINGS

For external use only. Flammable. Keep away from heat or flame.

DO NOT USE

- In children less than 2 months of age
- On open skin wounds.

When using this product keep out of eyes, ears and mouth. In case of contact with eyes, rinse eyes thoroughly with water.

Stop use and ask a doctor if irritation or rash occurs.

These may be signs of a serious condition.

Keep out of reach of children.

If swallowed, get medical help or contact a Poison Control Center right away.

Directions

- Place enough product on hands to cover all surfaces. Rub hands together until dry.
- Supervise children under 6 years of age when using this product to avoid swallowing.

OTHER INFORMATION

- Store between 15º - 30ºC (59-86F).
- Avoid freezing and excessive heat above 40ºC (104F)

INACTIVE INGREDIENTS

Glycerin, carbomer, triethanolamine, purified water USP, aloe vera.